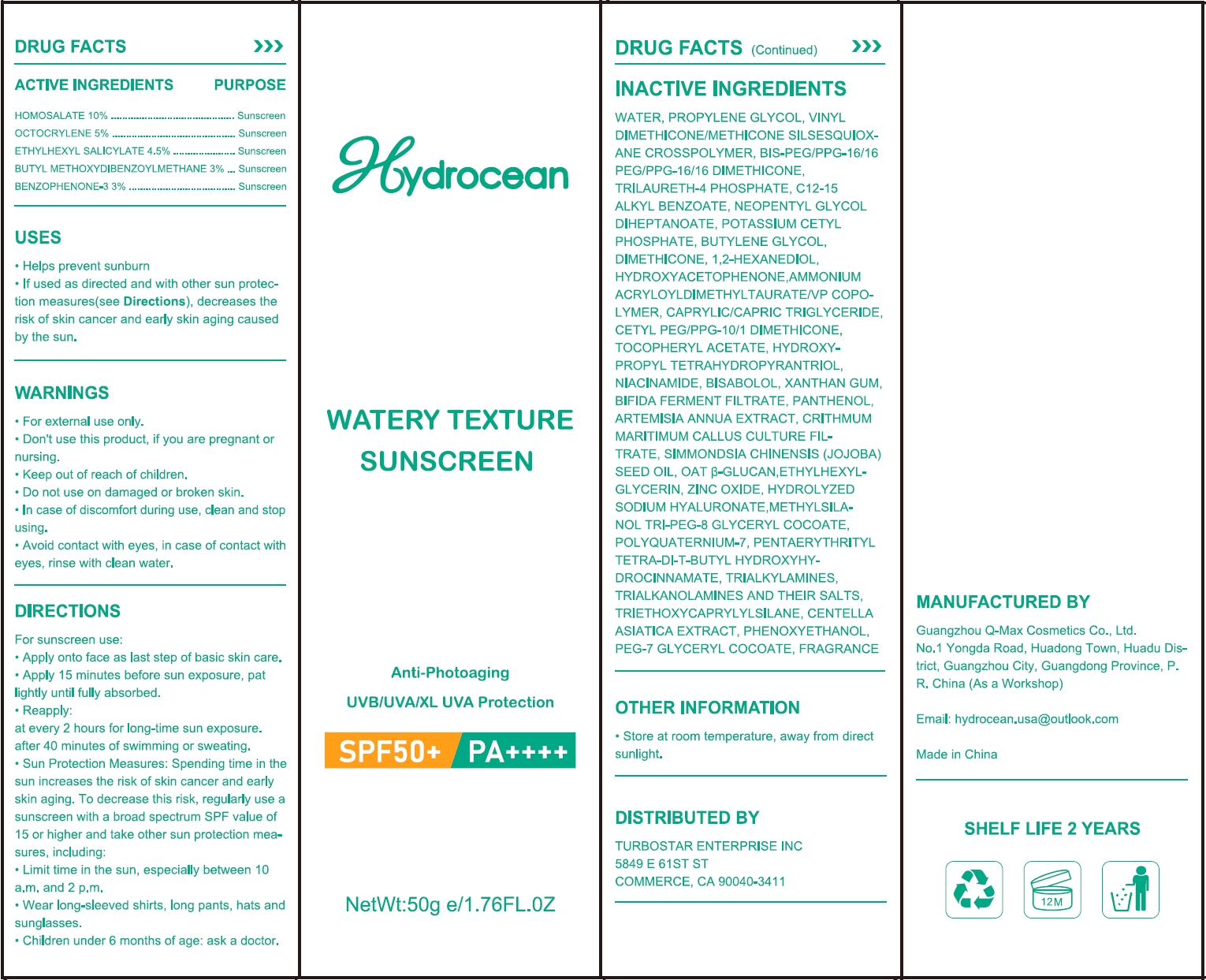 DRUG LABEL: WATERY TEXTURE SUNSCREEN
NDC: 84257-102 | Form: LOTION
Manufacturer: Guangzhou Maitelin Information Technology Co., Ltd.
Category: otc | Type: HUMAN OTC DRUG LABEL
Date: 20240627

ACTIVE INGREDIENTS: HOMOSALATE 10 g/100 g; OXYBENZONE 3 g/100 g; OCTOCRYLENE 5 g/100 g; OCTISALATE 4.5 g/100 g; AVOBENZONE 3 g/100 g
INACTIVE INGREDIENTS: VINYL DIMETHICONE/METHICONE SILSESQUIOXANE CROSSPOLYMER; BIS-PEG/PPG-16/16 PEG/PPG-16/16 DIMETHICONE; .ALPHA.-TOCOPHEROL ACETATE; PANTHENOL; PEG-7 GLYCERYL COCOATE; TROLAMINE; NIACINAMIDE; PENTAERYTHRITOL TETRAKIS(3-(3,5-DI-TERT-BUTYL-4-HYDROXYPHENYL)PROPIONATE); TRIALLYLAMINE; ARTEMISIA ANNUA FLOWERING TOP; POTASSIUM CETYL PHOSPHATE; HYDROXYACETOPHENONE; MEDIUM-CHAIN TRIGLYCERIDES; CETYL PEG/PPG-10/1 DIMETHICONE (HLB 5); TRIETHOXYCAPRYLYLSILANE; CENTELLA ASIATICA TRITERPENOIDS; FRAGRANCE FLORAL ORC0902236; WATER; POLYQUATERNIUM-7 (70/30 ACRYLAMIDE/DADMAC; 1600000 MW); BIFIDOBACTERIUM BIFIDUM; OAT; PHENOXYETHANOL; TRILAURETH-4 PHOSPHATE; AMMONIUM ACRYLOYLDIMETHYLTAURATE/VP COPOLYMER; DIMETHICONE; LEVOMENOL; JOJOBA OIL; HYALURONIC ACID; 1,2-HEXANEDIOL; BUTYLENE GLYCOL; XANTHAN GUM; HYDROXYPROPYL TETRAHYDROPYRANTRIOL; ETHYLHEXYLGLYCERIN; PROPYLENE GLYCOL; NEOPENTYL GLYCOL DIHEPTANOATE; ALKYL (C12-15) BENZOATE; CRITHMUM MARITIMUM WHOLE; ZINC OXIDE

WATERY TEXTURE SUNSCREEN

ACTIVE INGREDIENT

HOMOSALATE 10%
OCTOCRYLENE 5%
ETHYLHEXYL SALICYLATE 4.5%
BUTYL METHOXYDIBENZOYLMETHANE 3%
BENZOPHENONE-3 3%

PURPOSE

Sunscreen

Keep out of reach of children.

INDICATIONS AND USAGE

Helps prevent sunburn
If used as directed and with other sun protec-tion measures(see Directions), decreases therisk of skin cancer and early skin aging causedby the sun.

WARNINGS

For external use only.
Don't use this product, if you are pregnant or nursing.
Keep out of reach of children.
Do not use on damaged or broken skin.
In case of discomfort during use, cean and stop using.
Avoid contact with eyes, in case of contact with eyes, rinse with clean water.

DOSAGE AND ADMINISTRATION

Apply onto face as last step of basic skin care.
Apply 15 minutes before sun exposure, pat lightly until fully absorbed.
Reapply:
at every 2 hours for long-time sun exposure.
after 40 minutes of swimming or sweating.
Sun Protection Measures: Spending time in the sun increases the risk of skin cancer and earlyskin aging. To decrease this risk, regularly use asunscreen with a broad spectrum SPF value of15 or higher and take other sun protection mea-sures, including:Limit time in the sun, especially between 10a.m. and 2 p.m.
.Wear long-sleeved shirts, long pants, hats and sunglasses.
.Children under 6 months of age: ask a doctor.

STORAGE AND HANDLING

Store at room temperature, away from directsunlight.

INACTIVE INGREDIENT

WATER
PROPYLENE GLYCOL
VINYL DIMETHICONE/METHICONE SILSESQUIOXANE CROSSPOLYMER
BIS-PEG/PPG-16/16 PEG/PPG-16/16 DIMETHICONE
TRILAURETH-4 PHOSPHATE
C12-15 ALKYL BENZOATE
NEOPENTYL GLYCOL DIHEPTANOATE
POTASSIUM CETYL PHOSPHATE
BUTYLENE GLYCOL
DIMETHICONE
1,2-HEXANEDIOL
HYDROXYACETOPHENONE
AMMONIUM ACRYLOYLDIMETHYLTAURATE/VP COPOLYMER
CAPRYLIC/CAPRIC TRIGLYCERIDE
CETYL PEG/PPG-10/1 DIMETHICONE
TOCOPHERYL ACETATE
HYDROXYPROPYL TETRAHYDROPYRANTRIOL
NIACINAMIDE
BISABOLOL
XANTHAN GUM
BIFIDA FERMENT FILTRATE
PANTHENOL
ARTEMISIA ANNUA EXTRACT
CRITHMUM MARITIMUM CALLUS CULTURE FILTRATE
SIMMONDSIA CHINENSIS (JOJOBA) SEED OIL
OAT β-GLUCAN
ETHYLHEXYLGLYCERIN
ZINC OXIDE
HYDROLYZED SODIUM HYALURONATE
METHYLSILANOL TRI-PEG-8 GLYCERYL COCOATE
POLYQUATERNIUM-7
PENTAERYTHRITYL TETRA-DI-T-BUTYL HYDROXYHYDROCINNAMATE
TRIALKYLAMINES
TRIALKANOLAMINES AND THEIR SALTS
TRIETHOXYCAPRYLYLSILANE
CENTELLA ASIATICA EXTRACT
PHENOXYETHANOL
PEG-7 GLYCERYL COCOATE
FRAGRANCE